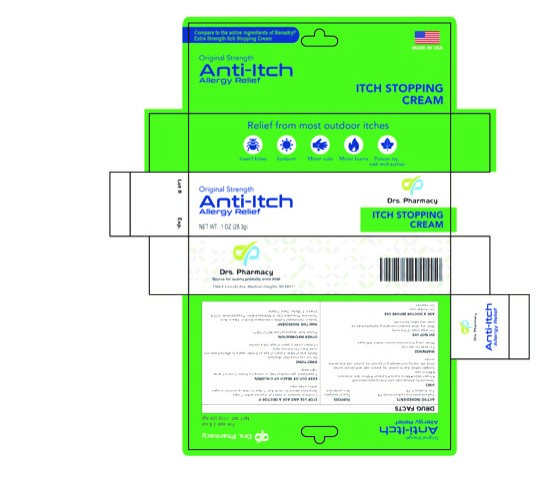 DRUG LABEL: ANTI-ITCH
NDC: 80489-005 | Form: CREAM
Manufacturer: OL PHARMA TECH, LLC
Category: otc | Type: HUMAN OTC DRUG LABEL
Date: 20250109

ACTIVE INGREDIENTS: DIPHENHYDRAMINE HYDROCHLORIDE 1 g/100 g; ZINC ACETATE 0.1 g/100 g
INACTIVE INGREDIENTS: DECYL OLEATE; TROLAMINE; EDETATE DISODIUM; WATER; PROPYLPARABEN; METHYLPARABEN; PROPYLENE GLYCOL; MINERAL OIL; SODIUM CETOSTEARYL SULFATE; CETOSTEARYL ALCOHOL; STEARIC ACID; .ALPHA.-TOCOPHEROL

Active Ingredients

Diphenhydramine hydrochloride 1%

Zinc Acetate 0.1%

Purpose

Topical analgesic

skin protectant

uses

temporarily relieves pain and itching associated with:

- insect bites
- minor burns
- sunburn
- minor skin irritations
- minor cuts
- scrapes
- rashes due to poison ivy, poison oak, and poison sumac
- dries the oozing and weeping of poison ivy, poison oak and poison sumac

warnings

For external use only

Ask a doctor before use

- on chicken pox
- on measles

Do Not Use

- on large areas of the body
- with any other product containing diphenhydramine, even one taken by mouth

When using this product avoid contact with eyes

Stop use and ask a doctor if

- condition worsens or does not improve within 7 days
- symptoms persist for more than 7 days or clear up and occur again within a few days

Keep out of reach of children. If swallowed, get medical help or contact a Poison Control Center right away.

Directions

Do not use more than directed:

- adults and children 2 years of age and older: apply to affected area not more than 3 to 4 times daily
- children under 2 years of age: ask a doctor

OTHER SAFETY INFORMATION

protect from excessive heat (40°C/104°F)

Inactive Ingredients

cetostearyl alcohol, sodium cetostearyl sulfate, stearic acid, trolamine, mineral oil, propylene glycol, water, methyl paraben, propyl paraben, EDTA, vitamin E

Questions

drspharmacyusa.com

Directions

do not use more than directed:

- adults and children 2 years of age and older: apply to affected area not more than 3 to 4 times daily
- children under 2 years of age: ask a doctor

PACKAGE LABEL

Itch stopping cream